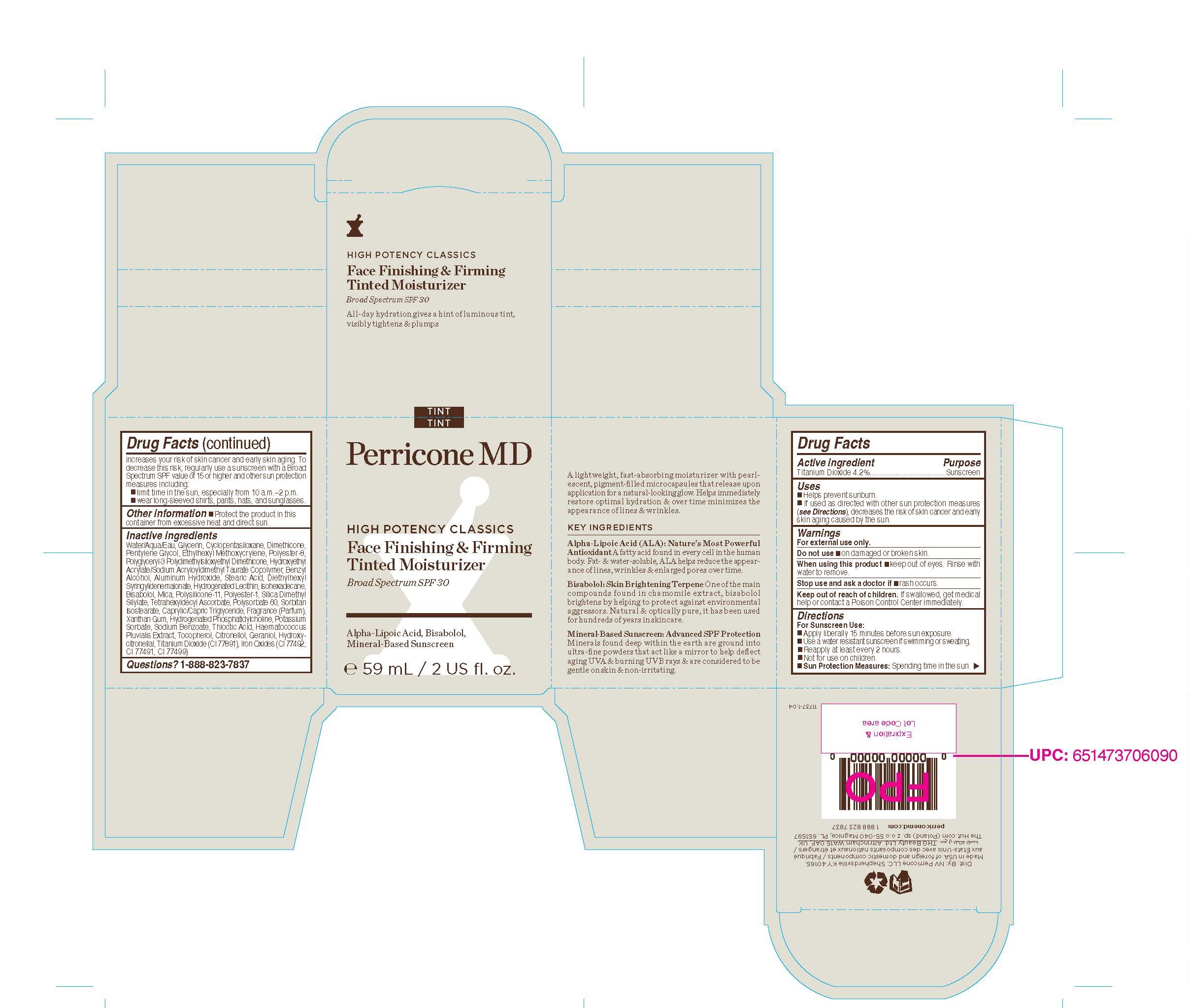 DRUG LABEL: Perricone MD HIGH POTENCY CLASSICS Face Finishing and Firming Tinted Moisturizer Broad Spectrum SPF 30
NDC: 84448-134 | Form: CREAM
Manufacturer: THG Beauty USA LLC
Category: otc | Type: HUMAN OTC DRUG LABEL
Date: 20251023

ACTIVE INGREDIENTS: TITANIUM DIOXIDE 4.2 g/100 mL
INACTIVE INGREDIENTS: DIMETHICONE; BISABOLOL; GLYCERIN; MICA; CI 77491; POLYSORBATE 60; CI 77499; PEGOTERATE; SILICA DIMETHYL SILYLATE; XANTHAN GUM; TOCOPHEROL; CITRONELLOL; CYCLOPENTASILOXANE; PENTYLENE GLYCOL; POLYGLYCERYL-3 POLYDIMETHYLSILOXYETHYL DIMETHICONE (4000 MPA.S); BENZYL ALCOHOL; HYDROGENATED SOYBEAN LECITHIN; STEARIC ACID; HYDROGENATED SOYBEAN PHOSPHATIDYLCHOLINE; POLYESTER-8 (1400 MW, CYANODIPHENYLPROPENOYL CAPPED); HYDROXYETHYL ACRYLATE/SODIUM ACRYLOYLDIMETHYL TAURATE COPOLYMER (45000 MPA.S AT 1%); DIETHYLHEXYL SYRINGYLIDENEMALONATE; TETRAHEXYLDECYL ASCORBATE; POTASSIUM SORBATE; ALUMINUM HYDROXIDE; SORBITAN ISOSTEARATE; DIMETHICONE/VINYL DIMETHICONE CROSSPOLYMER (SOFT PARTICLE); THIOCTIC ACID; SODIUM BENZOATE; CAPRYLIC/CAPRIC TRIGLYCERIDE; FRAGRANCE 13576; HAEMATOCOCCUS PLUVIALIS; GERANIOL; HYDROXYCITRONELLAL; WATER; ETHYLHEXYL METHOXYCRYLENE; ISOHEXADECANE; CI 77492

ACTIVE INGREDIENT

Titanium Dioxide 4.2%

PURPOSE

Sunscreen

Uses

■ Helps prevent sunburn.
■ If used as directed with other sun protection measures (see Directions), decreases the risk of skin cancer and early skin aging caused by the sun.

WARNINGS

For external use only.

Do not use ■ on damaged or broken skin.

When using this product ■ keep out of eyes. Rinse with water to remove.

Stop use and ask a doctor if ■ rash occurs.

Keep out of reach of children. If swallowed, get medical help or contact a Poison Control Center immediately.

Directions
For Sunscreen Use:
■ Apply liberally 15 minutes before sun exposure.
■ Use a water resistant sunscreen if swimming or sweating.
■ Reapply at least every 2 hours.
■ Not for use on children.
■ Sun Protection Measures: Spending time in the sun increases your risk of skin cancer and early skin aging. To decrease this risk, regularly use a sunscreen with a Broad Spectrum SPF value of 15 or higher and other sun protection measures including:
■ limit time in the sun, especially from 10 a.m.–2 p.m.
■ wear long-sleeved shirts, pants, hats, and sunglasses.

Other information ■ Protect the product in this container from excessive heat and direct sun.

INACTIVE INGREDIENT

Water/Aqua/Eau, Glycerin, Cyclopentasiloxane, Dimethicone, Pentylene Glycol, Ethylhexyl Methoxycrylene, Polyester-8, Polyglyceryl-3 Polydimethylsiloxyethyl Dimethicone, Hydroxyethyl Acrylate/Sodium Acryloyldimethyl Taurate Copolymer, Benzyl Alcohol, Aluminum Hydroxide, Stearic Acid, Diethylhexyl Syringylidenemalonate, Hydrogenated Lecithin, Isohexadecane, Bisabolol, Mica, Polysilicone-11, Polyester-1, Silica Dimethyl Silylate, Tetrahexyldecyl Ascorbate, Polysorbate 60, Sorbitan Isostearate, Caprylic/Capric Triglyceride, Fragrance (Parfum), Xanthan Gum, Hydrogenated Phosphatidylcholine, Potassium Sorbate, Sodium Benzoate, Thioctic Acid, Haematococcus Pluvialis Extract, Tocopherol, Citronellol, Geraniol, Hydroxycitronellal, Titanium Dioxide (CI 77891), Iron Oxides (CI 77492, CI 77491, CI 77499).

QUESTIONS

1-888-823-7837